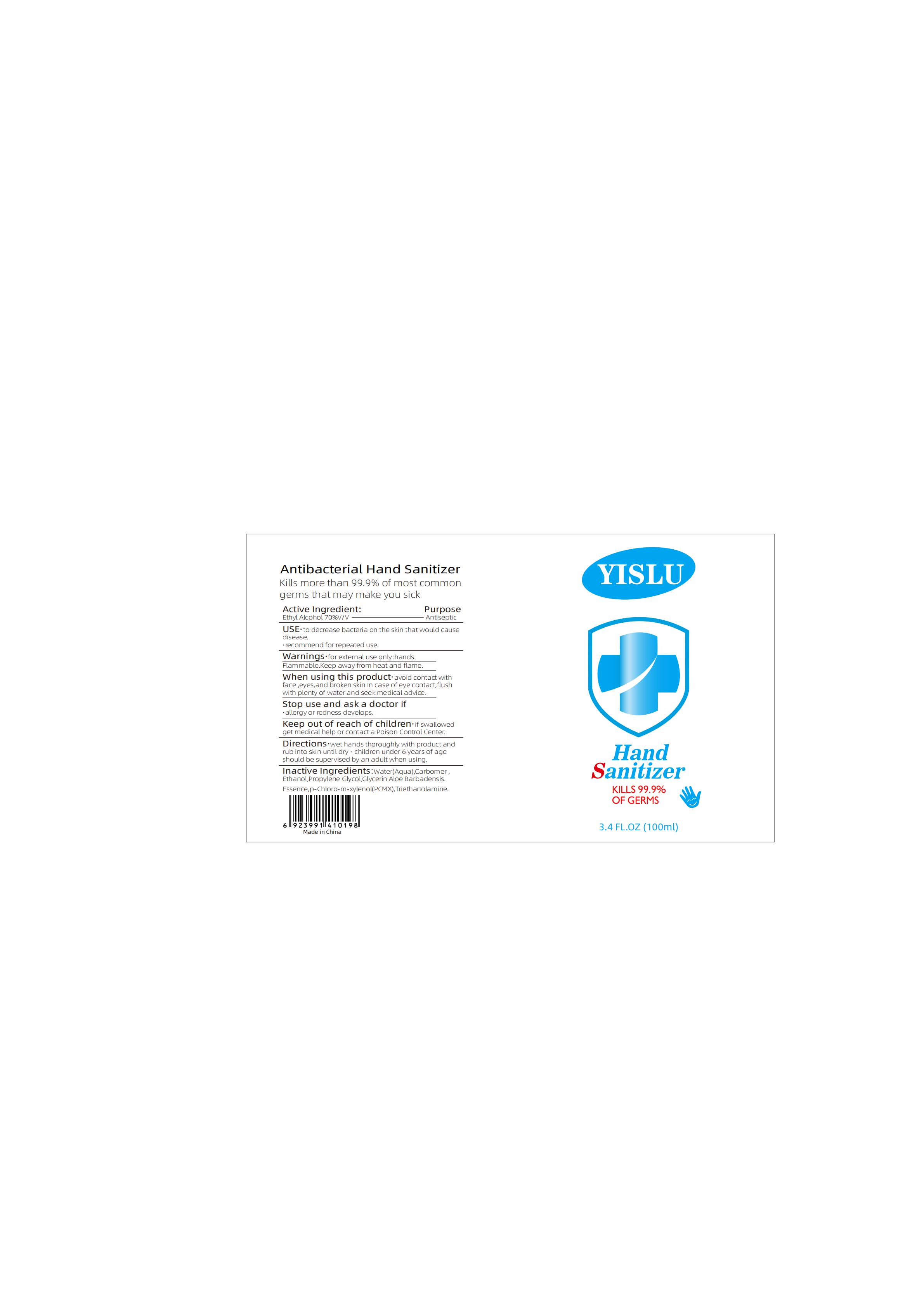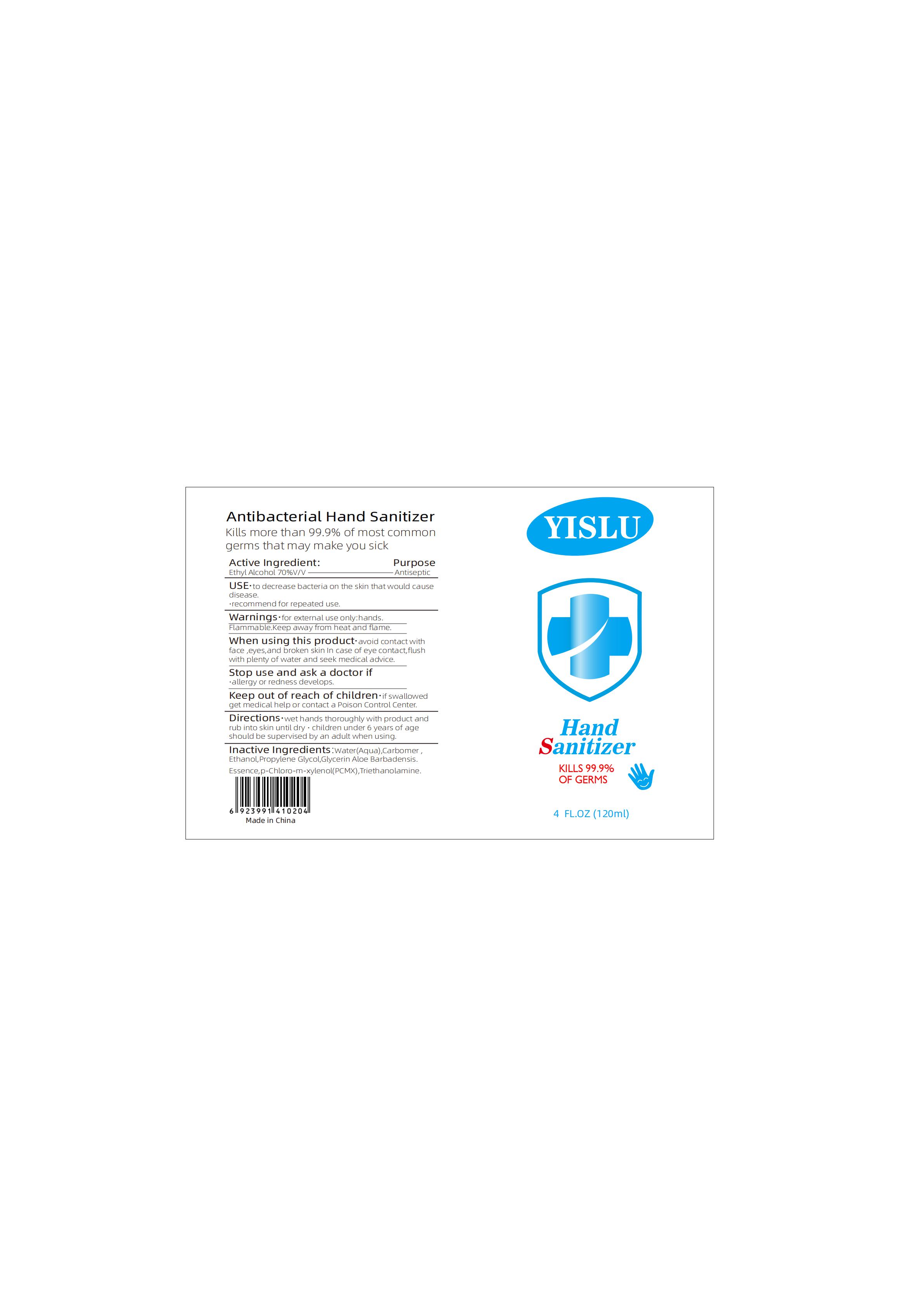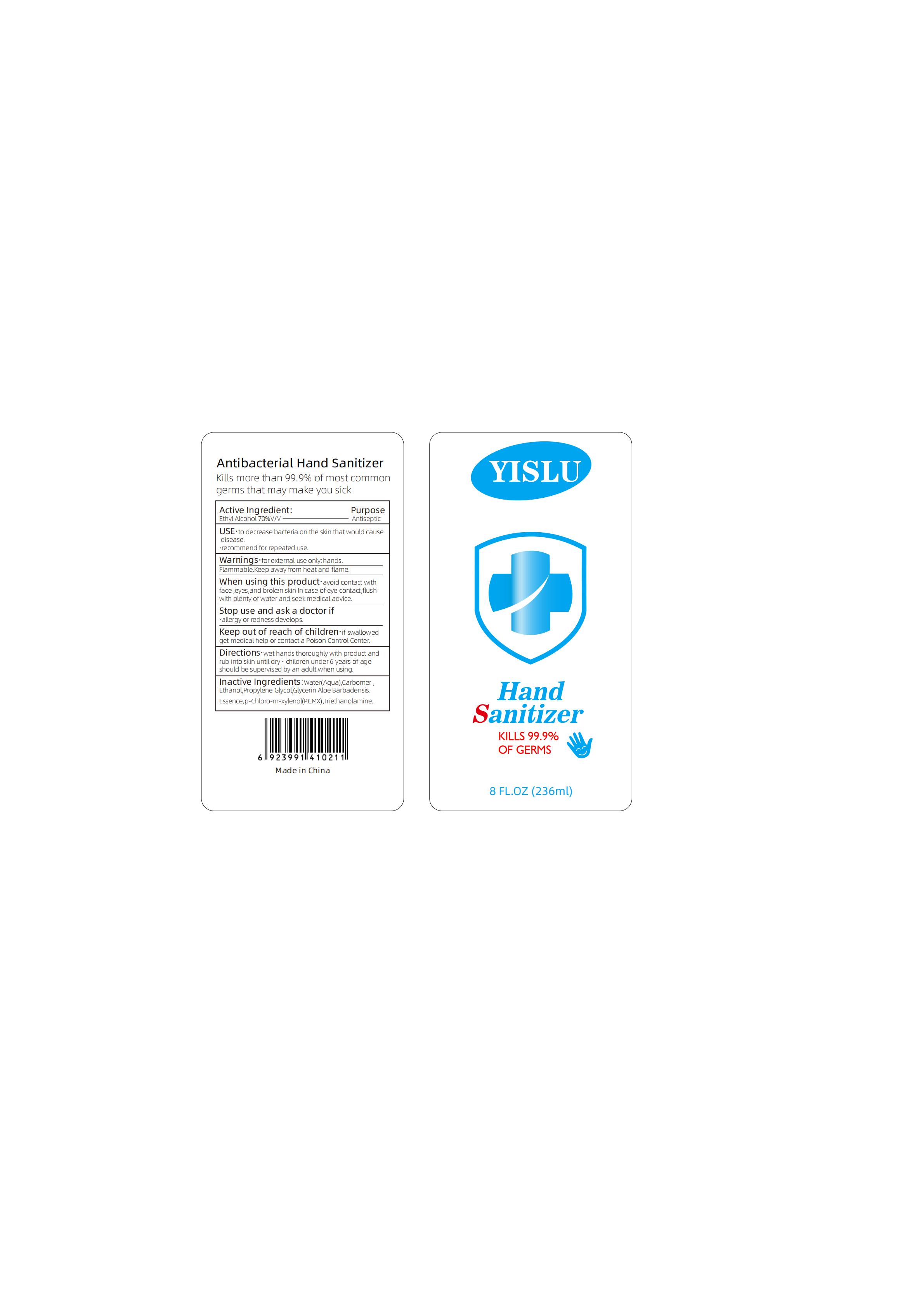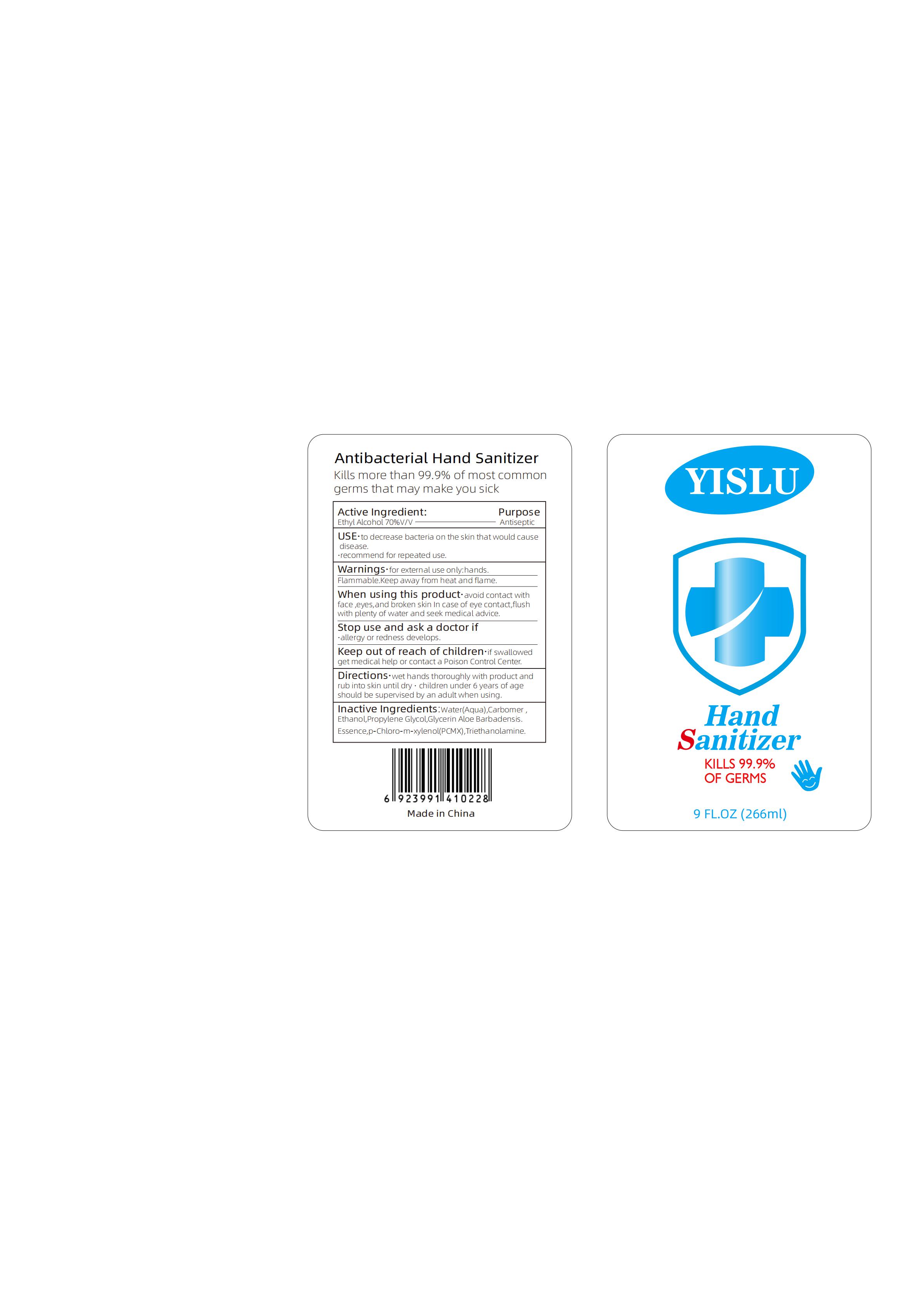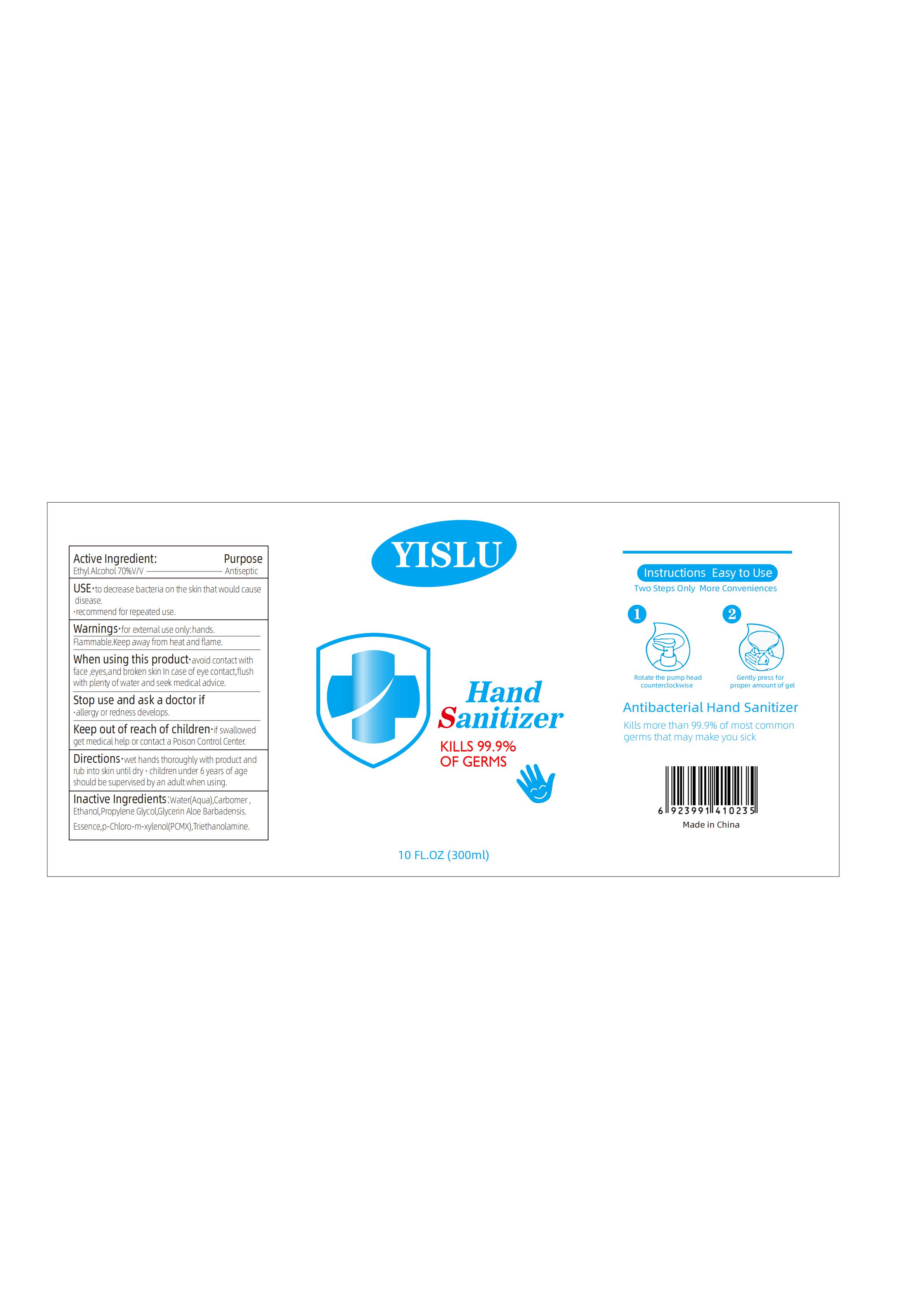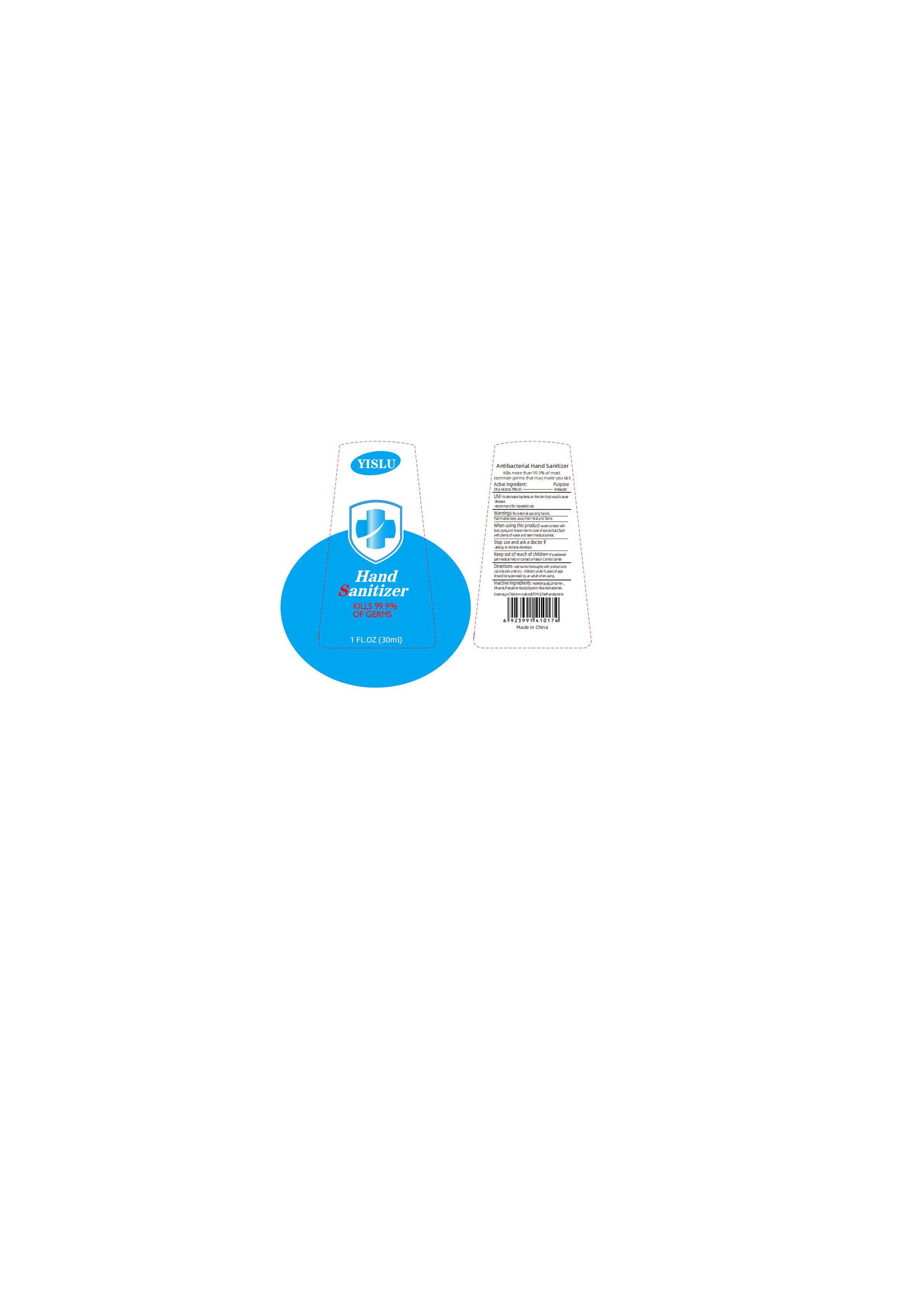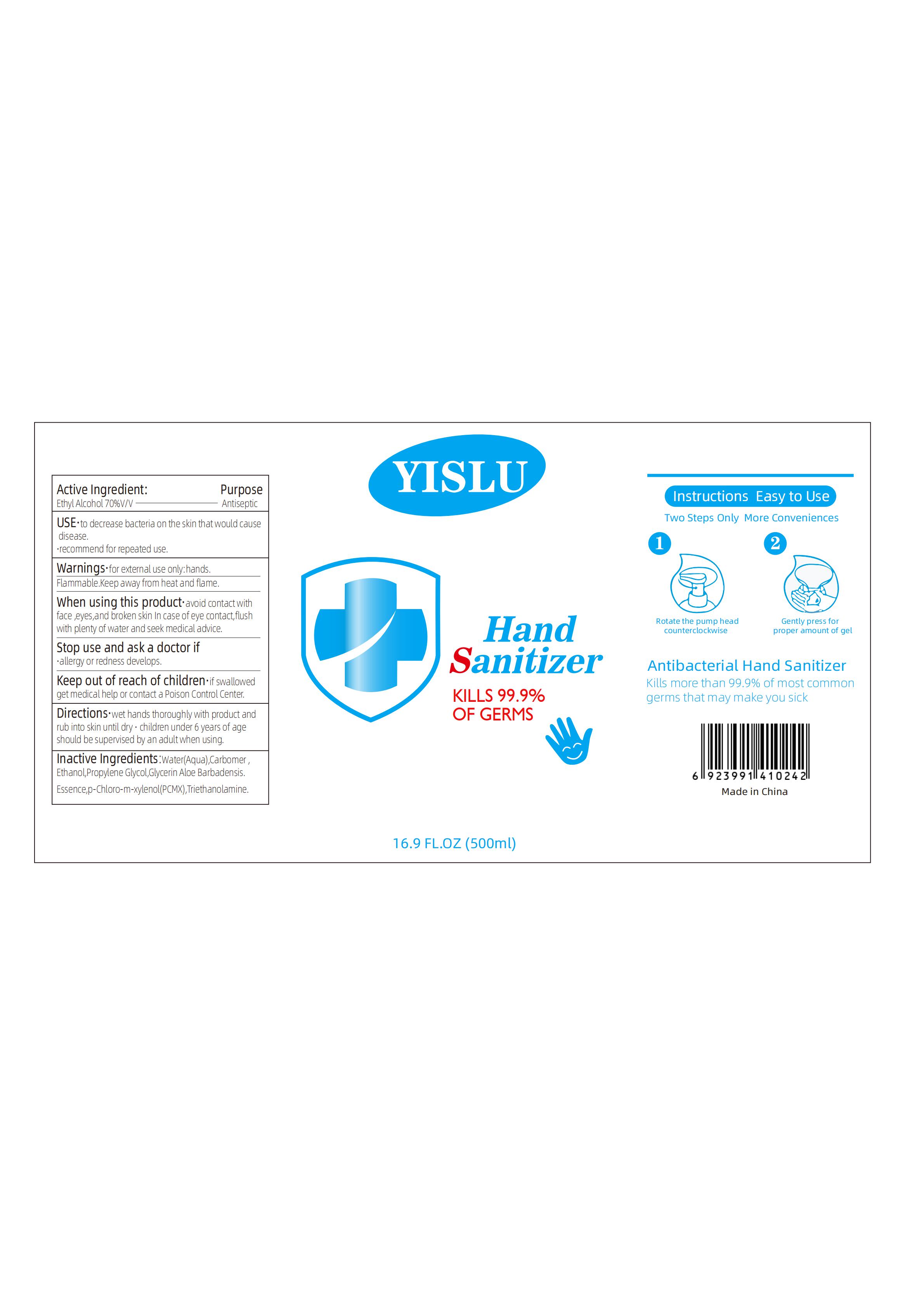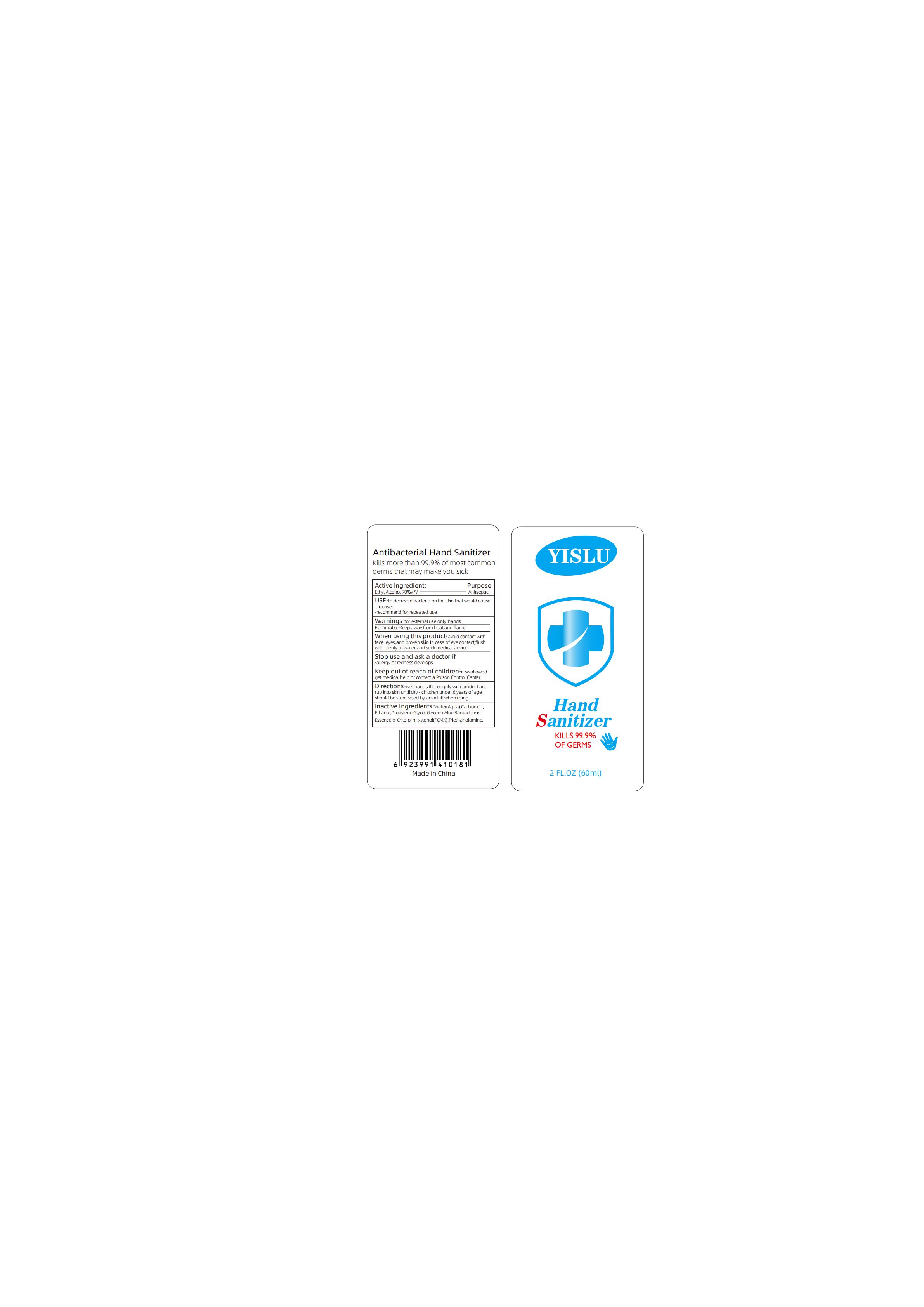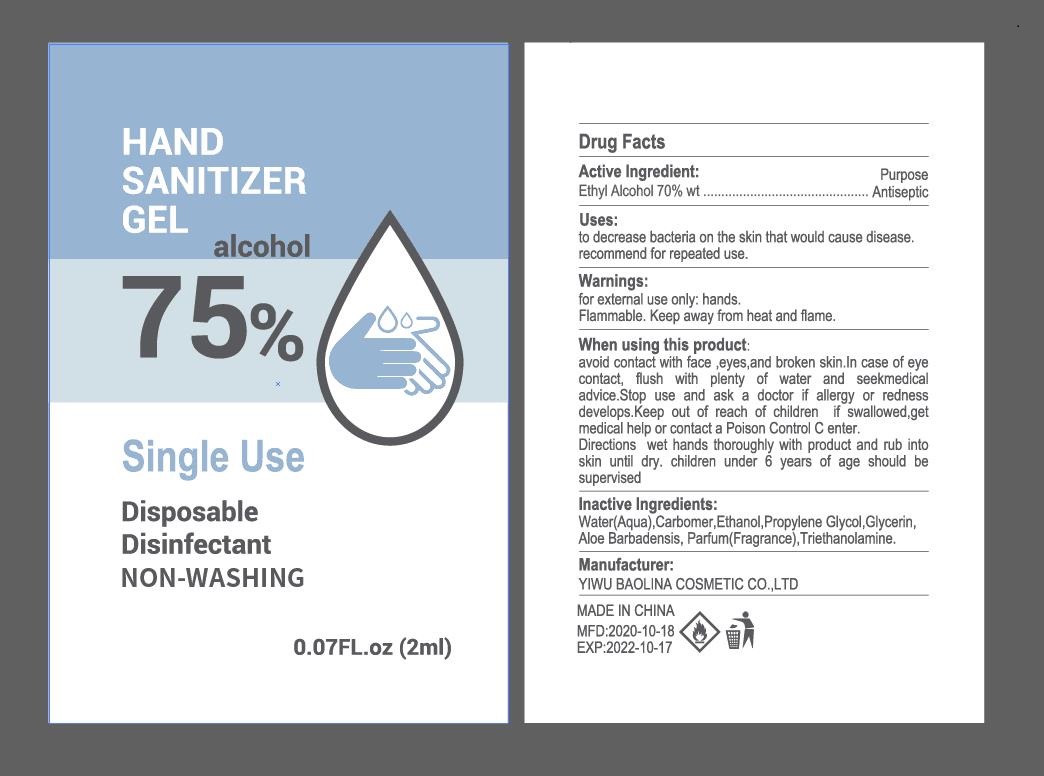 DRUG LABEL: Antibacterial Hand Sanitizer
NDC: 75273-006 | Form: GEL
Manufacturer: YIWU BAOLINA COSMETIC CO., LTD
Category: otc | Type: HUMAN OTC DRUG LABEL
Date: 20201019

ACTIVE INGREDIENTS: ALCOHOL 70 mL/100 mL
INACTIVE INGREDIENTS: GLYCERIN; CARBOMER 934; PROPYLENE GLYCOL; CHLOROXYLENOL; WATER; TROLAMINE

75273-006
Antibacterial Hand Sanitizer Gel

Active Ingredient(s)

Isopropyl Alcohol 70% v/v. Purpose: Antiseptic

Purpose

ANTISEPTIC

Use

TO DECREASE BACTERIA ON THE SKIN THET WOULD CAUSE DISEASE.RECOMMEND FOR REPEATED USE.

Warnings

FOR EXTERNAL USE ONLY:HANDS.FLAMMABLE.KEEP AWAY FROM HEAT AND FLAME.

Do not use

- in children less than 2 months of age
- on open skin wounds

WHEN USING THIS PRODUCT

AVOID CONTACT WITH FACE,EYES ,AND BROKEN SKIN IN CASE OF EYE CONTACT,FLUSH WITH PLENTY OF WATER AND SEEK MEDICAL ADVICE.

Stop use and ask a doctor if

ALLERGY OR REDNESS DEVELOPS.

Keep out of reach of children

If swallowed, get medical help or contact a Poison Control Center.

Directions

WET HANDS THOROUGHLY WITH PRODUCT AND RUB INTO SKIN UNTIL DRY .CHILDREN UNDER 6 YEARS OF AGE SHOULD BE SUPERVISED BY AN ADULT WHEN USING.

Other information

- Store between 15-30C (59-86F)
- Avoid freezing and excessive heat above 40C (104F)

Inactive ingredients

CARBOMER,CHLOROXYLENOL,WATER,,GLYCERIN,TROLAMINE,PROPYLENE GLYCOL.